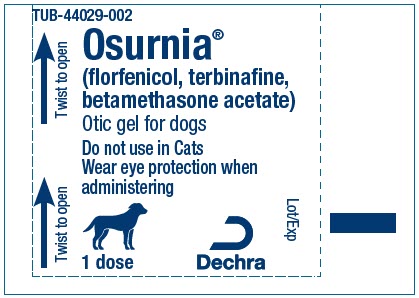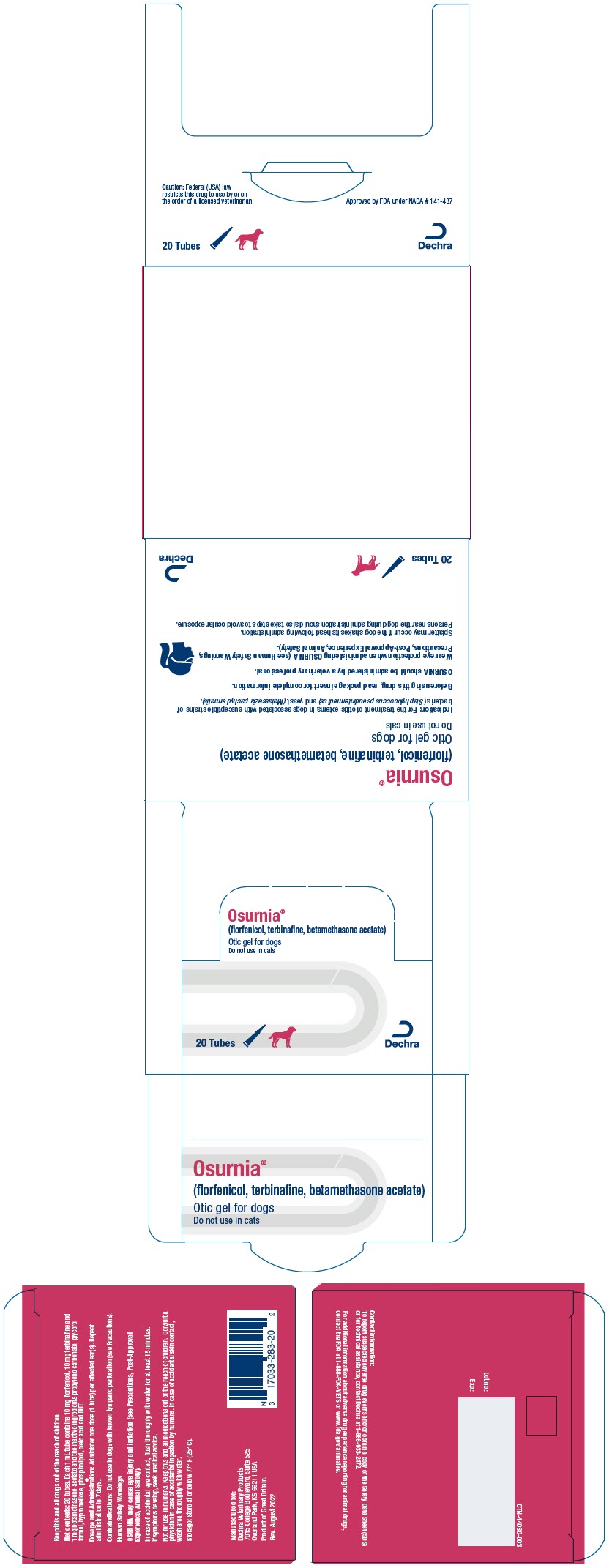 DRUG LABEL: Osurnia
NDC: 17033-283 | Form: GEL
Manufacturer: Dechra Veterinary Products
Category: animal | Type: PRESCRIPTION ANIMAL DRUG LABEL
Date: 20240208

ACTIVE INGREDIENTS: florfenicol 10 mg/1 mL; terbinafine 10 mg/1 mL; betamethasone acetate 1 mg/1 mL

Osurnia®
(florfenicol, terbinafine, betamethasone acetate)

Otic Gel

Antibacterial, antifungal, anti-inflammatory

For Otic Use in Dogs Only

Do not use in cats

CAUTION:

Federal (USA) law restricts this drug to use by or on the order of a licensed veterinarian.

DESCRIPTION:

OSURNIA contains 10 mg florfenicol, 10 mg terbinafine and 1 mg betamethasone acetate per mL and the inactive ingredients propylene carbonate, glycerol formal, hypromellose, phospholipid, oleic acid and BHT in an off-white to slightly yellow translucent gel.

INDICATION:

OSURNIA is indicated for the treatment of otitis externa in dogs associated with susceptible strains of bacteria (Staphylococcus pseudintermedius) and yeast (Malassezia pachydermatis).

DOSAGE AND ADMINISTRATION:

OSURNIA should be administered by a veterinary professional. Wear eye protection when administering Osurnia (see Human Safety Warnings, Precautions, Post-Approval Experience and Animal Safety).

Splatter may occur if the dog shakes its head following administration. Persons near the dog during administration should also take steps to avoid ocular exposure.

1. Clean and dry the external ear canal before administering the initial dose of the product.
2. Verify the tympanic membrane is intact prior to each administration (see Precautions, Contraindications, Animal Safety and Post-Approval Experience).
3. Administer one dose (1 tube) per affected ear(s) and repeat administration in 7 days.
4. Open tube by twisting the soft tip. Insert the flexible tip in the affected external ear canal(s) and squeeze entire tube contents into the external ear canal(s). After application, gently massage the base of the ear to allow the gel to penetrate the lower part of the ear canal.
5. Restrain dog to minimize post-application head shaking to reduce potential for splatter of product, and accidental eye exposure in people and dogs (see Post-Approval Experience and Animal Safety).
6. Do not clean the ear canal for 45 days after the initial administration to allow contact of the gel with the ear canal. Cleaning the ear may affect product effectiveness (see Effectiveness). If alternative otic therapies are required, it is recommended to clean the ear(s) before application.

CONTRAINDICATIONS:

Do not use in dogs with known tympanic perforation (see Precautions). Do not use in dogs with a hypersensitivity to florfenicol, terbinafine or corticosteroids.

WARNINGS:

Human Safety Warnings:

OSURNIA may cause eye injury and irritation (see Precautions, Post-Approval Experience and Animal Safety).

In case of accidental eye contact, flush thoroughly with water for at least 15 minutes. If symptoms develop, seek medical advice.

Not for use in humans. Keep this and all medications out of reach of children. Consult a physician in case of accidental ingestion by humans. In case of accidental skin contact, wash area thoroughly with water.

PRECAUTIONS:

Wear eye protection when administering OSURNIA and restrain the dog to minimize post-application head shaking. Reducing the potential for splatter of product will help prevent accidental eye exposure in people and dogs and help to prevent ocular injury (see Human Safety Warnings, Post-Approval Experience and Animal Safety).

The use of OSURNIA in dogs with perforated tympanic membranes has not been evaluated. The integrity of the tympanic membrane should be confirmed before administering this product. Reevaluate the dog if hearing loss or signs of vestibular dysfunction are observed during treatment.

Proper patient selection is important when considering the benefits and risks of using OSURNIA. The integrity of the tympanic membrane should be confirmed before administering each dose of product.

Changes to the middle ear, such as ulceration of the mucosal lining, have been associated with OSURNIA administration. (see Animal Safety).

Signs of tympanic membrane rupture, internal ear disease such as head tilt, ataxia, nystagmus, facial paralysis, and keratoconjunctivitis sicca have also been reported (see Post-Approval Experience).

Do not administer orally.

Use of topical otic corticosteroids has been associated with adrenocortical suppression and iatrogenic hyperadrenocorticism in dogs (see Animal Safety).

Use with caution in dogs with impaired hepatic function (see Animal Safety and Adverse Reactions).

The safe use of OSURNIA in dogs used for breeding purposes, during pregnancy, or in lactating bitches, has not been evaluated.

ADVERSE REACTIONS:

The following adverse reactions were reported during the course of a US field study for treatment of otitis externa in dogs treated with OSURNIA with 1 tube per affected ear(s) and repeated after 7 days:

Frequency of Adverse Reaction by Treatment
Adverse Reaction | OSURNIA (n=190) | Placebo (n=94)
Elevated Alkaline Phosphatase | 15 (7.9%) | 3 (3.2%)
Vomiting | 7 (3.7%) | 1 (1.1%)
Elevated AST, ALT, ALP [Aspartate aminotransferase (AST), alanine aminotransferase (ALT), alkaline phosphatase (ALP). Two dogs with pre-existing elevations in ALP were reported to have an increase in liver enzymes (ALP, ALT and/or AST) at study exit. Subsequent clinical chemistries returned to pre-treatment levels in one dog, while no follow-up was performed for the second dog.] | 2 (1.1%) | 0 (0.0%)
Weight loss (>10% body weight) | 1 (0.53%) | 0 (0.0%)
Hearing Decrease/Loss | 1 (0.53%) | 1 (1.1%)

Post-Approval Experience (2020)

The following adverse events are based on post-approval adverse drug experience reporting for OSURNIA. Not all adverse events are reported to FDA/CVM. It is not always possible to reliably estimate the adverse event frequency or establish a causal relationship to product exposure using this data.

In humans, accidental exposure leading to corneal ulcers and other ocular injuries such as eye irritation, burning, stinging, and itchiness have been reported to occur when the dog shook its head after application of OSURNIA.

In dogs, the adverse events reported for OSURNIA are presented below in decreasing order of reporting frequency:

Deafness, ear discharge, pinnal irritation and ear pain, emesis, head shaking, internal ear disorder (head tilt and vestibular), ataxia, vocalization, corneal ulcer, keratoconjunctivitis sicca, nystagmus, tympanic rupture, and cranial nerve disorder (facial paralysis).

OSURNIA is not approved for use in cats. The adverse events reported following extra-label use in cats are presented below in decreasing order of reporting frequency:

Ataxia, anorexia, Horner's syndrome (third eyelid prolapse and miosis), internal ear disorder (head tilt and vestibular), anisocoria, lethargy, head shake, emesis, nystagmus, deafness, and tympanic rupture.

CONTACT INFORMATION:

To report suspected adverse drug events and/or obtain a copy of the Safety Data Sheet (SDS) or for technical assistance, contact Dechra at 1-866-933-2472

For additional information about adverse drug experience reporting for animal drugs, contact the FDA at 1-888-FDA-VETS or www.fda.gov/reportanimalae.

INFORMATION FOR DOG OWNERS:

Owners should be aware that adverse reactions may occur following administration of OSURNIA and should observe dog for signs such as deafness, ear pain and irritation, vomiting, head shaking, head tilt, incoordination, eye pain and ocular discharge (see Animal Safety and Post-Approval Experience). Owners should be advised to contact their veterinarian if any of the above signs are observed.

Owners should also be informed that splatter may occur if the dog shakes its head following administration of OSURNIA which may lead to ocular exposure. As a result, eye injuries in humans and dogs have been reported including corneal ulcers. Owners should be careful to avoid ocular exposure (see Precautions and Post-Approval Experience).

CLINICAL PHARMACOLOGY:

OSURNIA is a fixed combination of three active substances: florfenicol (antibacterial), terbinafine (antifungal) and betamethasone acetate (steroidal anti-inflammatory). Florfenicol is a bacteriostatic antibiotic which acts by inhibiting protein synthesis. Its spectrum of activity includes Gram-positive and Gram-negative bacteria. Terbinafine is an antifungal which selectively inhibits the early synthesis of ergosterol. Betamethasone acetate is a glucocorticosteroid with anti-inflammatory activity.

OSURNIA dissolves in ear wax and is slowly eliminated from the ear mechanically. Ear inflammation can increase the percutaneous absorption of active substances in OSURNIA.

In a laboratory study conducted in healthy dogs (see Animal Safety), low plasma concentrations of florfenicol, terbinafine, and betamethasone acetate were measurable during the first 2-4 days after administration of 1× dose, and during the first 2-7 days after administration of 5× dose. No quantifiable plasma concentrations of any of the three active ingredients were observed in the pre-dose samples of most dogs prior to second and third administrations. Although total and peak exposure in the blood tended to be highly variable between dogs, systemic drug concentrations tended to increase in a less than dose-proportional manner as the administered dose increased from 1× to 5×.

MICROBIOLOGY:

The compatibility and additive effect of each of the components in OSURNIA was demonstrated in a component effectiveness and non-interference study. An in vitro study of organisms collected from clinical cases of otitis externa in dogs determined that florfenicol and terbinafine inhibit the growth of bacteria and yeast commonly associated with otitis externa in dogs. No consistent synergistic or antagonistic effect of the two antimicrobials was demonstrated. The addition of betamethasone acetate to the combination did not impair antimicrobial activity to any clinically significant extent.

In a field study (see Effectiveness), the minimum of 10 isolates from successfully treated cases with OSURNIA was met for Staphylococcus pseudintermedius, Malassezia pachydermatis, and Pseudomonas aeruginosa. However, there were only three dogs where P. aeruginosa was the only pathogen cultured and they were all treatment failures. Therefore, OSURNIA may not be effective in treating otitis externa in which P. aeruginosa is the only pathogen present.

EFFECTIVENESS:

Effectiveness was evaluated in 235 dogs with otitis externa. The study was a double-masked field study with a placebo control (vehicle without the active ingredients). One hundred and fifty-nine dogs were treated with OSURNIA and seventy-six dogs were treated with the placebo control. All dogs were evaluated for safety. Treatment (1 mL) was administered to the affected ear(s) and repeated 7 days later. Prior to the first administration, the ear(s) were cleaned with saline but not prior to the Day 7 administration. Six clinical signs associated with otitis externa were evaluated: pain, erythema, exudate, swelling, odor and ulceration. Total clinical scores were assigned for a dog based on the severity of each clinical sign on Days 0, 7, 14, 30 and 45. Success was determined by clinical improvement at Day 45. The success rates of the two groups were significantly different (p=0.0094); 64.78% of dogs administered OSURNIA were successfully treated, compared to 43.42% of the dogs in the placebo control group.

ANIMAL SAFETY:

In a target animal safety study, 24 mixed breed dogs (4 dogs/sex/group) were aurally administered 0×, 1× (1 mL/ear or 2 mL/dog with repeated administration in 7 days) or 5× (5 mL/ear or 10 mL/dog with repeated administration in 7 days) doses of OSURNIA for a total of 6 administrations in 5 weeks. All dogs remained in good health with normal hearing throughout the study. Decreased weight gain was noted in the 1× and 5× groups compared to the control group. Clinical findings included post-administration ear wetness in 1× and 5× groups and unilateral, transient brown/red discharge from one ear each in two 5× dogs, with erythema in one dog after the 4th application. Local microscopic changes in ears (without clinical effects) included: slight or moderate unilateral vesicle formation within the epithelium of the tympanic membrane in two 1× and four 5× dogs, and unilateral mucosal ulceration in the lining of the middle ear cavity in three 5× dogs. Three 5× dogs had slightly elevated ALT activity, accompanied by minimal or mild microscopic hepatocellular vacuolation (in two dogs). Cortisol response to ACTH stimulation was decreased, but within the normal reference range, in 1× dogs. The 5× dogs had a decrease in serum cortisol levels after ACTH stimulation (below normal reference range) accompanied by decreased adrenal gland and thymic weights with minimal adrenal cortical atrophy and slight (in three dogs) or moderate (in one dog also noted with slightly lower lymphocyte counts) lymphoid depletion of the thymus. The ACTH stimulation test results are consistent with systemic absorption of betamethasone resulting in a likely reversible suppression of the hypothalamic-pituitary-adrenal axis as seen with administration of exogenous corticosteroids.

STORAGE CONDITIONS:

Store at or below 77° F (25° C).

HOW SUPPLIED:

OSURNIA is a gel in a single-use tube with a flexible soft tip, supplied in cartons containing 2 or 20 tubes.

Approved by FDA under NADA # 141-437

MANUFACTURED FOR:
Dechra Veterinary Products
7015 College Boulevard, Suite 525
Overland Park, KS 66211 USA

Product of Great Britain

OSURNIA® is a registered trademark of Dechra Limited.

Rev. August 2022 PIL-44029-003

PRINCIPAL DISPLAY PANEL - 1 Dose Tube Label

TUB-44029-002
Twist to open

Osurnia®
(florfenicol, terbinafine,
betamethasone acetate)

Otic gel for dogs

Do not use in Cats

Wear eye protection when
administering

1 dose

Dechra

Lot/Exp

PRINCIPAL DISPLAY PANEL - 20 Tube Carton

Osurnia®

(florfenicol, terbinafine, betamethasone acetate)

Otic gel for dogs

Do not use in cats

20 Tubes

Dechra